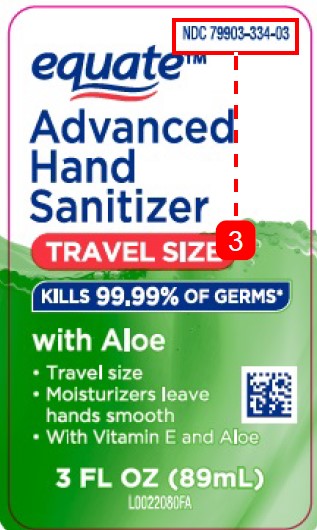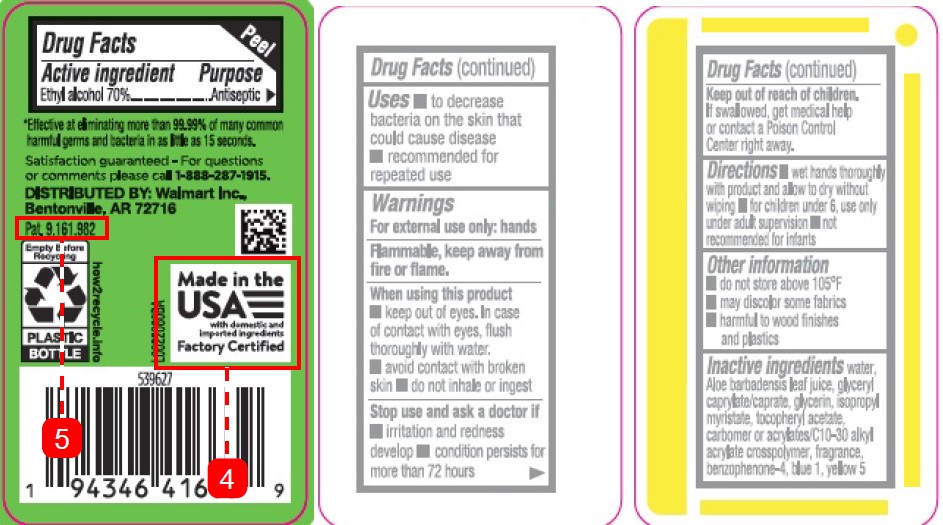 DRUG LABEL: Advanced Hand Sanitizer
NDC: 79903-334 | Form: GEL
Manufacturer: Walmart Inc.
Category: otc | Type: HUMAN OTC DRUG LABEL
Date: 20260227

ACTIVE INGREDIENTS: ALCOHOL 70 mL/100 mL
INACTIVE INGREDIENTS: WATER; ALOE VERA LEAF; GLYCERYL CAPRYLATE/CAPRATE; GLYCERIN; ISOPROPYL MYRISTATE; .ALPHA.-TOCOPHEROL ACETATE; CARBOMER INTERPOLYMER TYPE A (ALLYL SUCROSE CROSSLINKED); SULISOBENZONE; FD&C BLUE NO. 1; FD&C YELLOW NO. 5

Equate 439.001/439AB-AC rev 1
Advanced Hand Sanitizer with Aloe

Active ingredient

Ethyl Alcohol 70%

Purpose

Antiseptic

Uses

- to decrease bacteria on the skin that could cause disease
- recommended for repeated use

Warnings

For external use only: hands

Flammable. Keep away from fire or flame.

When using this product

- keep out of eyes. In case of contact with eyes, flush thoroughly with water
- avoid contact with broken skin
- do not inhale or ingest

Stop use and ask a doctor if

- irritation and redness develop
- conditiion persists for more than 72 hours

Keep out of reach of children.

If swallowed, get medical help or contact a Poison Control Center right away.

Directions

- wet hands thoroughly with product and allow to dry without wiping
- for children under 6, use only under adult supervision
- not recommended for infants

Other information

- do not store above 105ºF
- may discolor some fabrics
- harmful to wood finishes and plastics

INACTIVE INGREDIENTS

water, Aloe barbadensis leaf juice, glyceryl caprylate/caprate, glycerin, isopropyl myristate, tocopheryl acetate, carbomer or acrylates/C10-30 alkyl acrylate crosspolymer, fragrance, benzophenone-4, blue 1, yellow 5

Claims

*Effective at eliminating more than 99.99% of many common harmful germs and bacteria in as little as 15 seconds.

ADVERSE REACTION

Satisfaction guaranteed - For questions or comments please call 1-888-287-1915.

DISTRIBUTED BY: Walmart Inc.,

Bentonville, AR 72716

Pat. 9,161,982

Empty Before Recycling

PLASTIC BOTTLE

how2recycle.info

Made in the USA with domestic and imported ingredients

Factory Certified

PRINCIPAL DISPLAY PANEL

NDC 79903-334-03

equate ™

Advanced

Hand Sanitizer

TRAVEL SIZE

KILLS 99.99& OF GERMS*

with Aloe

- Travel size
- Moisturizers leave hands smooth
- With Vitamin E and Aloe

3 FL OZ (89mL)